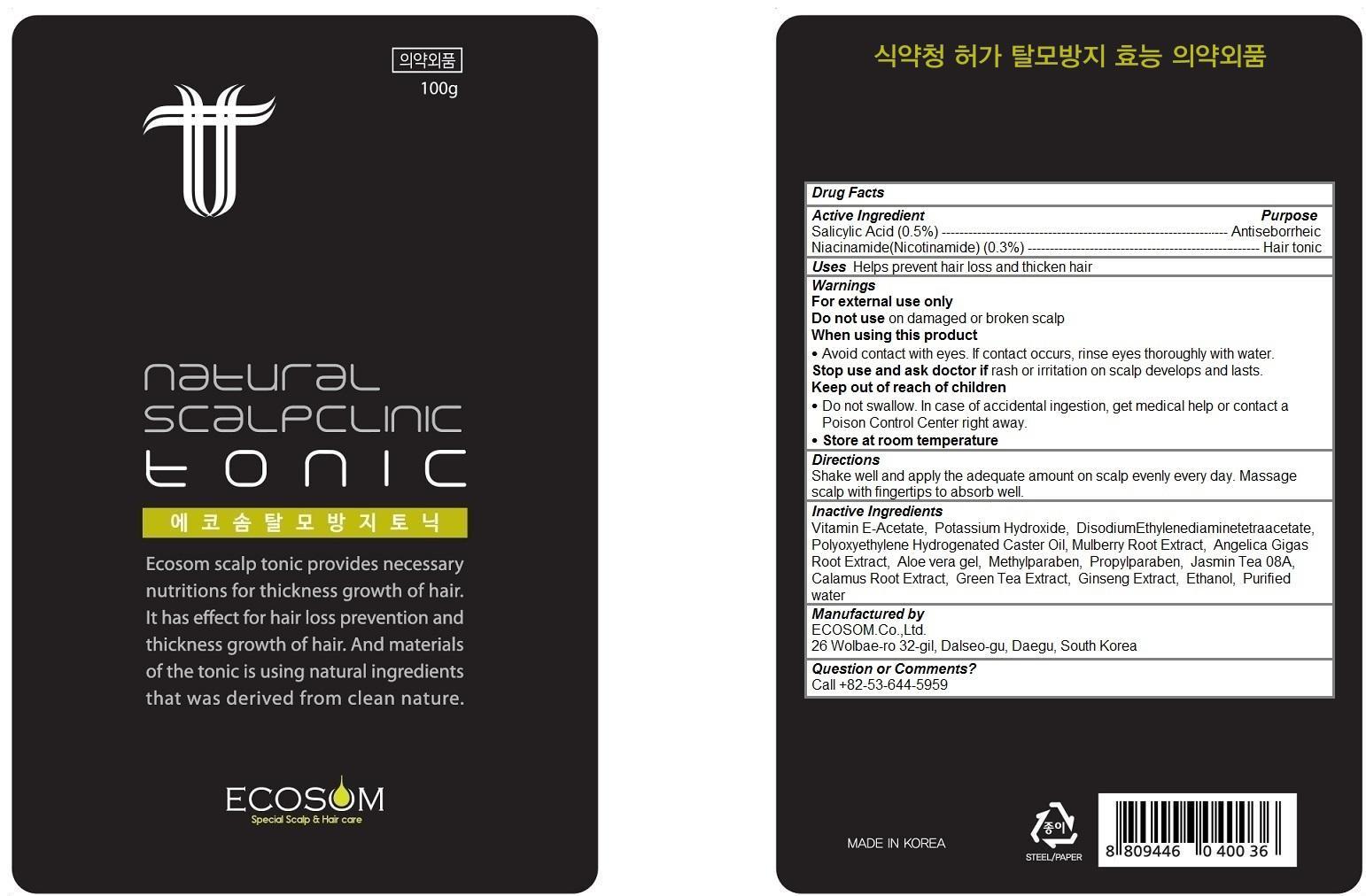 DRUG LABEL: Ecosom Tonic
NDC: 69856-102 | Form: LIQUID
Manufacturer: ECOSOM.Co.,Ltd.
Category: otc | Type: HUMAN OTC DRUG LABEL
Date: 20150601

ACTIVE INGREDIENTS: NIACINAMIDE 0.3 1/100 g; SALICYLIC ACID 0.5 1/100 g
INACTIVE INGREDIENTS: .ALPHA.-TOCOPHEROL ACETATE; Potassium Hydroxide; EDETATE DISODIUM; PEG-10 HYDROGENATED CASTOR OIL; WHITE MULBERRY; ANGELICA GIGAS ROOT; ALOE VERA LEAF; METHYLPARABEN; Propylparaben; JASMINUM OFFICINALE LEAF; JATEORHIZA CALUMBA ROOT; GREEN TEA LEAF; ASIAN GINSENG; ALCOHOL; water

Ecosom Tonic